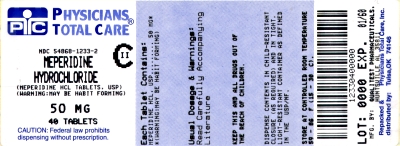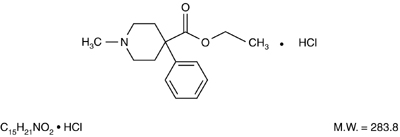 DRUG LABEL: Meperidine Hydrochloride
NDC: 54868-1233 | Form: TABLET
Manufacturer: Physicians Total Care, Inc.
Category: prescription | Type: HUMAN PRESCRIPTION DRUG LABEL
Date: 20120306
DEA Schedule: CII

ACTIVE INGREDIENTS: MEPERIDINE HYDROCHLORIDE 50 mg/1 1
INACTIVE INGREDIENTS: CELLULOSE, MICROCRYSTALLINE; STARCH, CORN; SODIUM STARCH GLYCOLATE TYPE A POTATO; STEARIC ACID

MEPERIDINE HYDROCHLORIDE TABLETS, USP

CII

WARNING: May be habit forming

Rx only

DESCRIPTION

Meperidine hydrochloride is a white crystalline substance with a melting point of 186°C to 189°C. It is readily soluble in water and has a neutral reaction and a slightly bitter taste. The solution is not decomposed by a short period of boiling.

Each tablet, for oral administration, contains 50 mg or 100 mg meperidine hydrochloride. In addition, each tablet contains the following inactive ingredients: microcrystalline cellulose, pregelatinized starch, sodium starch glycolate and stearic acid.

Chemically, meperidine hydrochloride is 4-Piperidinecarboxylic acid, 1-methyl-4-phenyl-, ethyl ester, hydrochloride and has the following structure:

CLINICAL PHARMACOLOGY

Meperidine hydrochloride is a narcotic analgesic with multiple actions qualitatively similar to those of morphine; the most prominent of these involve the central nervous system and organs composed of smooth muscle. The principal actions of therapeutic value are analgesia and sedation.

There is some evidence which suggests that meperidine may produce less smooth muscle spasm, constipation, and depression of the cough reflex than equianalgesic doses of morphine.

INDICATIONS AND USAGE

Meperidine hydrochloride tablets are indicated for the relief of moderate to severe pain.

CONTRAINDICATIONS

Meperidine hydrochloride tablets are contraindicated in patients with hypersensitivity to meperidine or to any of its ingredients.

Meperidine is contraindicated in patients who are receiving monoamine oxidase (MAO) inhibitors or those who have recently received such agents. Therapeutic doses of meperidine have occasionally precipitated unpredictable, severe, and occasionally fatal reactions in patients who have received such agents within 14 days. The mechanism of these reactions is unclear, but may be related to a preexisting hyperphenylalaninemia. Some have been characterized by coma, severe respiratory depression, cyanosis, and hypotension, and have resembled the syndrome of acute narcotic overdose. Serotonin syndrome with agitation, hyperthermia, diarrhea, tachycardia, sweating, tremors and impaired consciousness may also occur. In other reactions the predominant manifestations have been hyperexcitability, convulsions, tachycardia, hyperpyrexia, and hypertension. Although it is not known that other narcotics are free of the risk of such reactions, virtually all of the reported reactions have occurred with meperidine. If a narcotic is needed in such patients, a sensitivity test should be performed in which repeated, small, incremental doses of morphine are administered over the course of several hours while the patient's condition and vital signs are under careful observation. (Intravenous hydrocortisone or prednisolone have been used to treat severe reactions, with the addition of intravenous chlorpromazine in those cases exhibiting hypertension and hyperpyrexia. The usefulness and safety of narcotic antagonists in the treatment of these reactions is unknown.)

Meperidine hydrochloride tablets are contraindicated in patients with severe respiratory insufficiency (see WARNINGS: Respiratory Conditions).

WARNINGS

Meperidine should not be used for treatment of chronic pain. Meperidine should only be used in the treatment of acute episodes of moderate to severe pain. Prolonged meperidine use may increase the risk of toxicity (e.g., seizures) from the accumulation of the meperidine metabolite, normeperidine.

Meperidine hydrochloride tablets are opioid agonists and a Schedule II controlled substance with an abuse liability similar to morphine.

Meperidine hydrochloride tablets can be abused in a manner similar to other opioid agonists, legal or illicit. This should be considered when prescribing or dispensing meperidine hydrochloride tablets in situations where the physician or pharmacist is concerned about an increased risk of misuse, abuse, or diversion.

Misuse, Abuse, and Diversion of Opioids

Meperidine is an opioid agonist of the morphine-type. Such drugs are sought by drug abusers and people with addiction disorders and are subject to criminal diversion.

Meperidine can be abused in a manner similar to other opioid agonists, legal or illicit. This should be considered when prescribing or dispensing meperidine hydrochloride tablets in situations where the physician or pharmacist is concerned about an increased risk of misuse, abuse, or diversion.

Meperidine hydrochloride tablets have been reported as being abused by crushing, chewing, snorting, or injecting the dissolved product. These practices will result in the uncontrolled delivery of the opioid and pose a significant risk to the abuser that could result in overdose or death (see WARNINGS and DRUG ABUSE AND ADDICTION).

Concerns about abuse, addiction, and diversion should not prevent the proper management of pain.

Healthcare professionals should contact their State Professional Licensing Board or State Controlled Substances Authority for information on how to prevent and detect abuse or diversion of this product.

Interactions with Alcohol and Drugs of Abuse

Meperidine may be expected to have additive effects when used in conjunction with alcohol, other opioids, or illicit drugs that cause central nervous system depression.

Head Injury and Increased Intracranial Pressure

The respiratory depressant effects of meperidine and its capacity to elevate cerebrospinal fluid pressure may be markedly exaggerated in the presence of head injury, other intracranial lesions, or a preexisting increase in intracranial pressure. Furthermore, narcotics produce adverse reactions which may obscure the clinical course of patients with head injuries. In such patients, meperidine must be used with extreme caution and only if its use is deemed essential.

Respiratory Conditions

Meperidine should be used with extreme caution in patients having an acute asthmatic attack, patients with chronic obstructive pulmonary disease or cor pulmonale, patients having a substantially decreased respiratory reserve, and patients with preexisting respiratory depression, hypoxia, or hypercapnia. In such patients, even usual therapeutic doses of narcotics may decrease respiratory drive while simultaneously increasing airway resistance to the point of apnea.

Hypotensive Effect

The administration of meperidine may result in severe hypotension in the postoperative patient or any individual whose ability to maintain blood pressure has been compromised by a depleted blood volume or the administration of drugs such as the phenothiazines or certain anesthetics.

Usage in Ambulatory Patients

Meperidine may impair the mental and/or physical abilities required for the performance of potentially hazardous tasks such as driving a car or operating machinery. The patient should be cautioned accordingly.

Meperidine, like other narcotics, may produce orthostatic hypotension in ambulatory patients.

Usage in Pregnancy

Meperidine should not be used in pregnant women prior to the labor period, unless in the judgment of the physician the potential benefits outweigh the possible risks, because safe use in pregnancy prior to labor has not been established relative to possible adverse effects on fetal development.

Labor and Delivery

Meperidine crosses the placental barrier and can produce depression of respiration and psychophysiologic functions in the newborn. Resuscitation may be required (see OVERDOSAGE). Therefore meperidine is not recommended during labor.

Nursing Mothers

Meperidine appears in the milk of nursing mothers receiving the drug. Due to the potential for serious adverse reactions in nursing infants, a decision should be made whether to discontinue nursing or to discontinue the drug, taking into account the potential benefits of the drug to the nursing woman.

PRECAUTIONS

General

Opioid analgesics can have a narrow therapeutic index in certain patient populations, particularly when combined with CNS depressant drugs. The use of these products should be reserved for cases where the benefits of opioid analgesia outweigh the known risks of respiratory depression, altered mental state, and postural hypotension.

Use of meperidine hydrochloride tablets may be associated with increased potential risks and should be used with caution in the following conditions: sickle cell anemia, pheochromocytoma, acute alcoholism; adrenocortical insufficiency (e.g., Addison's disease); CNS depression or coma; delirium tremens; debilitated patients; kyphoscoliosis associated with respiratory depression; myxedema or hypothyroidism; prostatic hypertrophy or urethral stricture; severe impairment of hepatic, pulmonary, or renal function; and toxic psychosis (see PRECAUTIONS: Special Risk Patients).

The administration of meperidine may obscure the diagnosis or clinical course in patients with acute abdominal conditions. All opioids may induce or aggravate seizures in some clinical settings.

Interactions with Other CNS Depressants

Meperidine hydrochloride tablets should be used with caution and consideration should be given to starting with a reduced dosage in patients who are concurrently receiving other central nervous system depressants including sedatives or hypnotics, general anesthetics, phenothiazines, other tranquilizers, and alcohol. Drug-drug interactions may result in respiratory depression, hypotension, profound sedation, coma, or death if these drugs are taken in combination with the usual doses of meperidine hydrochloride tablets.

Interactions with Mixed Agonist/Antagonist Opioid Analgesics

Agonist/antagonist analgesics (i.e., pentazocine, nalbuphine, butorphanol, and buprenorphine) should be administered with caution to a patient who has received or is receiving a course of therapy with a pure opioid agonist analgesic such as meperidine. In this situation, mixed agonist/antagonist analgesics may reduce the analgesic effect of meperidine and/or may precipitate withdrawal symptoms in these patients due to competitive blocking of receptors.

Supraventricular Tachycardias

Meperidine should be used with caution in patients with atrial flutter and other supraventricular tachycardias because of a possible vagolytic action which may produce a significant increase in the ventricular response rate.

Convulsions

Meperidine may aggravate preexisting convulsions in patients with convulsive disorders. If dosage is escalated substantially above recommended levels because of tolerance development, convulsions may occur in individuals without a history of convulsive disorders.

Acute Abdominal Conditions

The administration of meperidine or other narcotics may obscure the diagnosis or clinical course in patients with acute abdominal conditions.

Tolerance and Physical Dependence

Meperidine has the potential to produce tolerance and drug dependence. Tolerance is the need for increasing doses of opioids to maintain a defined effect such as analgesia (in the absence of disease progression or other external factors). Physical dependence is manifested by withdrawal symptoms after abrupt discontinuation of a drug or upon administration of an antagonist. Physical dependence and tolerance are not unusual during chronic opioid therapy.

The opioid abstinence or withdrawal syndrome is characterized by some or all of the following: restlessness, lacrimation, rhinorrhea, yawning, perspiration, chills, myalgia, mydriasis. Other symptoms also may develop, including: irritability, anxiety, backache, joint pain, weakness, abdominal cramps, insomnia, nausea, anorexia, vomiting, diarrhea, or increased blood pressure, respiratory rate, or heart rate.

In general, opioids used regularly should not be abruptly discontinued.

Use in Drug and Alcohol Addiction

Meperidine hydrochloride tablets are opioids with no approved use in the management of addictive disorders. Its proper usage in individuals with drug or alcohol dependence, either active or in remission, is for the management of pain requiring opioid analgesia. Meperidine hydrochloride tablets should be used with caution in patients with alcoholism and other drug dependencies due to the increased frequency of narcotic tolerance, dependence, and the risk of addiction observed in these patient populations. Abuse of meperidine hydrochloride tablets in combination with other CNS depressant drugs can result in serious risk to the patient.

Information for Patients/Caregivers

If clinically advisable, patients receiving meperidine hydrochloride tablets or their caregivers should be given the following information by the physician, nurse, pharmacist, or caregiver:

1. Patients should be aware that meperidine hydrochloride tablets contain meperidine, which is a morphine-like substance.
2. Patients should be advised to report pain and adverse experiences occurring during therapy. Individualization of dosage is essential to make optimal use of this medication.
3. Patients should be advised not to adjust the dose of meperidine hydrochloride tablets without consulting the prescribing professional.
4. Patients should be advised that meperidine hydrochloride tablets may impair mental and/or physical ability required for the performance of potentially hazardous tasks (e.g., driving, operating heavy machinery).
5. Patients should not combine meperidine hydrochloride tablets with alcohol or other central nervous system depressants (sleep aids, tranquilizers) except by the orders of the prescribing physician, because dangerous additive effects may occur, resulting in serious injury or death.
6. Women of childbearing potential who become, or are planning to become pregnant should be advised to consult their physician regarding the effects of analgesics and other drug use during pregnancy on themselves and their unborn child.
7. Patients should be advised that meperidine hydrochloride tablets are a potential drug of abuse. They should protect them from theft, and they should never be given to anyone other than the individual for whom they were prescribed.
8. Patients should be advised that if they have been receiving treatment with meperidine hydrochloride tablets for more than a few weeks and cessation of therapy is indicated, it may be appropriate to taper the meperidine hydrochloride tablets dose, rather than abruptly discontinue it, due to the risk of precipitating withdrawal symptoms. Their physician can provide a dose schedule to accomplish a gradual discontinuation of the medication.
9. Patients should be instructed to keep meperidine hydrochloride tablets in a secure place out of the reach of children. When meperidine hydrochloride tablets are no longer needed, the unused tablets should be destroyed by flushing down the toilet.

Drug Interactions

Also see WARNINGS.

Acyclovir

Plasma concentrations of meperidine and its metabolite, normeperidine, may be increased by acyclovir, thus caution should be used with concomitant administration.

Cimetidine

Cimetidine reduced the clearance and volume of distribution of meperidine and also the formation of the metabolite, normeperidine, in healthy subjects and thus, caution should be used with concomitant administration.

CNS Depressants

Concomitant use of CNS depressants with usual doses of meperidine may result in respiratory depression, hypotension, profound sedation, coma or death (see PRECAUTIONS: Interactions with Other CNS Depressants).

Phenytoin

The hepatic metabolism of meperidine may be enhanced by phenytoin. Concomitant administration resulted in reduced half-life and bioavailability with increased clearance of meperidine in healthy subjects, however, blood concentrations of normeperidine were increased, thus exercise caution when phenytoin is used concomitantly with meperidine.

Ritonavir

Plasma concentrations of the active metabolite normeperidine may be increased by ritonavir, thus concomitant administration should be avoided.

Opioid analgesics, including meperidine hydrochloride tablets, may enhance the neuromuscular blocking action of skeletal muscle relaxants and produce an increased degree of respiratory depression.

Special Risk Patients

Meperidine should be given with caution and the initial dose should be reduced in certain patients such as the elderly or debilitated, and those with severe impairment of hepatic or renal function, Sickle Cell Anemia, hypothyroidism, Addison's disease, Pheochromocytoma and prostatic hypertrophy or urethral stricture. In patients with pheochromocytoma, meperidine has been reported to provoke hypertension.

Usage in Hepatically Impaired Patients

Accumulation of meperidine and/or its active metabolite, normeperidine, can occur in patients with hepatic impairment. Meperidine should therefore be used with caution in patients with hepatic impairment.

Usage in Renally Impaired Patients

Accumulation of meperidine and/or its active metabolite, normeperidine, can also occur in patients with renal impairment. Meperidine should therefore be used with caution in patients with renal impairment.

Carcinogenesis, Mutagenesis, Impairment of Fertility

Studies to assess the carcinogenic or mutagenic potential of meperidine have not been conducted. Studies to determine the effect of meperidine on fertility have not been conducted.

Pregnancy

Pregnancy Category C:

Animal reproduction studies have not been conducted with meperidine. It is also not known whether meperidine hydrochloride tablets can cause fetal harm when administered to a pregnant woman or can affect reproduction capacity. Meperidine hydrochloride tablets should be given to a pregnant woman only if clearly needed.

Labor and Delivery

See WARNINGS.

Nursing Mothers

See WARNINGS.

Pediatric Use

The safety and effectiveness of meperidine in pediatric patients has not been established. Literature reports indicate that meperidine has a slower elimination rate in neonates and young infants compared to older children and adults. Neonates and young infants may also be more susceptible to the effects, especially the respiratory depressant effects. If meperidine use is contemplated in neonates or young infants, any potential benefits of the drug need to be weighed against the relative risk of the patient.

Geriatric Use

Clinical studies of meperidine hydrochloride tablets during product development did not include sufficient numbers of subjects aged 65 and over to evaluate age-related differences in safety or efficacy. Literature reports indicate that geriatric patients have a slower elimination rate compared to young patients and they may be more susceptible to the effects of meperidine. Reducing the total daily dose of meperidine is recommended in elderly patients and the potential benefits of the drug should be weighed against the relative risk to a geriatric patient.

ADVERSE REACTIONS

The major hazards of meperidine, as with other narcotic analgesics, are respiratory depression and, to a lesser degree, circulatory depression; respiratory arrest, shock, and cardiac arrest have occurred.

The most frequently observed adverse reactions include lightheadedness, dizziness, sedation, nausea, vomiting, and sweating. These effects seem to be more prominent in ambulatory patients and in those who are not experiencing severe pain. In such individuals, lower doses are advisable. Some adverse reactions in ambulatory patients may be alleviated if the patient lies down.

Other adverse reactions include:

Nervous System: Mood changes (e.g., euphoria, dysphoria), weakness, headache, agitation, tremor, involuntary muscle movements (e.g., muscle twitches, myoclonus), severe convulsions, transient hallucinations and disorientation, confusion, delirium, visual disturbances.

Gastrointestinal: Dry mouth, constipation, biliary tract spasm.

Cardiovascular: Flushing of the face, tachycardia, bradycardia, palpitation, hypotension (see WARNINGS), syncope.

Genitourinary: Urinary retention.

Allergic: Pruritus, urticaria, other skin rashes, wheal and flare over the vein with intravenous injection. Hypersensitivity reactions, anaphylaxis.

Histamine release leading to hypotension and/or tachycardia, flushing, sweating, and pruritus.

DRUG ABUSE AND ADDICTION

Meperidine hydrochloride tablets contain meperidine, a mu-agonist opioid with an abuse liability similar to morphine and is a Schedule II controlled substance. Meperidine, like morphine and other opioids used in analgesia, can be abused and is subject to criminal diversion.

Drug addiction is characterized by compulsive use, use for non-medical purposes, and continued use despite harm or risk of harm. Drug addiction is a treatable disease, utilizing a multi-disciplinary approach, but relapse is common.

"Drug seeking" behavior is very common in addicts and drug abusers. Drug-seeking tactics include emergency calls or visits near the end of office hours, refusal to undergo appropriate examination, testing or referral, repeated "loss" of prescriptions, tampering with prescriptions and reluctance to provide prior medical records or contact information for other treating physician(s). "Doctor shopping" to obtain additional prescriptions is common among drug abusers and people suffering from untreated addiction.

Abuse and addiction are separate and distinct from physical dependence and tolerance. Physicians should be aware that addiction may not be accompanied by concurrent tolerance and symptoms of physical dependence in all addicts. In addition, abuse of opioids can occur in the absence of true addiction and is characterized by misuse for non-medical purposes, often in combination with other psychoactive substances. Meperidine hydrochloride tablets, like other opioids, have been diverted for non-medical use. Careful record-keeping of prescribing information, including quantity, frequency, and renewal requests is strongly advised.

Abuse of meperidine hydrochloride tablets poses a risk of overdose and death. This risk is increased with concurrent abuse of meperidine hydrochloride tablets with alcohol and other substances. Due to the presence of talc as one of the excipients in tablets, parenteral abuse of crushed tablets can be expected to result in local tissue necrosis, infection, pulmonary granulomas, and increased risk of endocarditis and valvular heart disease. In addition, parenteral drug abuse is commonly associated with transmission of infectious diseases such as hepatitis and HIV.

Proper assessment of the patient, proper prescribing practices, periodic re-evaluation of therapy, and proper dispensing and storage are appropriate measures that help to limit abuse of opioid drugs.

OVERDOSAGE

Symptoms

Serious overdosage with meperidine is characterized by respiratory depression (a decrease in respiratory rate and/or tidal volume, Cheyne-Stokes respiration, cyanosis), extreme somnolence progressing to stupor or coma, skeletal muscle flaccidity, hypothermia, cold and clammy skin, and sometimes bradycardia and hypotension. In severe overdosage, particularly by the intravenous route, apnea, circulatory collapse, cardiac arrest, and death may occur.

Treatment

Primary attention should be given to the reestablishment of adequate respiratory exchange through provision of a patent airway and institution of assisted or controlled ventilation. The narcotic antagonist, naloxone hydrochloride, is a specific antidote against respiratory depression which may result from overdosage or unusual sensitivity to narcotics, including meperidine. Therefore, an appropriate dose of this antagonist should be administered as necessary, preferably by the intravenous route, simultaneously with efforts at respiratory resuscitation.

An antagonist should not be administered in the absence of clinically significant respiratory or cardiovascular depression.

Oxygen, intravenous fluids, vasopressors, and other supportive measures should be employed as indicated.

In cases of overdosage with meperidine hydrochloride tablets, the stomach should be evacuated by emesis or gastric lavage.

NOTE: In an individual physically dependent on narcotics, the administration of the usual dose of a narcotic antagonist will precipitate an acute withdrawal syndrome. The severity of this syndrome will depend on the degree of physical dependence and the dose of antagonist administered. The use of narcotic antagonists in such individuals should be avoided if possible. If a narcotic antagonist must be used to treat serious respiratory depression in the physically dependent patient, the antagonist should be administered with extreme care and only one-fifth to one-tenth the usual initial dose administered.

DOSAGE AND ADMINISTRATION

For Relief of Pain

Dosage should be adjusted according to the severity of the pain and the response of the patient. Meperidine is less effective orally than on parenteral administration. The dose of meperidine hydrochloride tablets should be proportionately reduced (usually by 25 to 50 percent) when administered concomitantly with phenothiazines and many other tranquilizers since they potentiate the action of meperidine hydrochloride tablets.

Adults

The usual dosage is 50 mg to 150 mg orally, every 3 or 4 hours as necessary.

Pediatric Patients

The usual dosage is 1.1 mg/kg to 1.8 mg/kg orally, up to the adult dose, every 3 or 4 hours as necessary (see PRECAUTIONS: Pediatric Use).

SAFETY AND HANDLING

Meperidine hydrochloride tablets are a dosage form that contains meperidine hydrochloride which is a controlled substance. Like morphine, meperidine is controlled under Schedule II of the Controlled Substances Act. Meperidine, like all opioids, is liable to diversion and misuse and should be handled accordingly. Patients and their families should be instructed to flush any meperidine hydrochloride tablets that are no longer needed.

Meperidine hydrochloride tablets have been targeted for theft and diversion by criminals. Healthcare professionals should contact their State Professional Licensing Board or State Controlled Substance Authority for information on how to prevent and detect abuse or diversion of this product.

HOW SUPPLIED

Meperidine HCl Tablets of 50 mg, white, round, convex, bisected tablets, debossed "4171" over "V" on one side and plain on the reverse side, are available in bottles of

Bottles of 10 | NDC 54868-1233-1
Bottles of 20 | NDC 54868-1233-6
Bottles of 30 | NDC 54868-1233-3
Bottles of 40 | NDC 54868-1233-2
Bottles of 100 | NDC 54868-1233-4
Bottles of 120 | NDC 54868-1233-5

STORAGE AND HANDLING

Dispense in a tight, light-resistant container as defined in the USP.

Store at 20° to 25°C (68° to 77°F) [see USP Controlled Room Temperature].

Manufactured for:
QUALITEST PHARMACEUTICALS
Huntsville, AL 35811

8181647
R12/11-R7

Relabeling and Repackaging by:
Physicians Total Care, Inc.
Tulsa, Oklahoma 74146